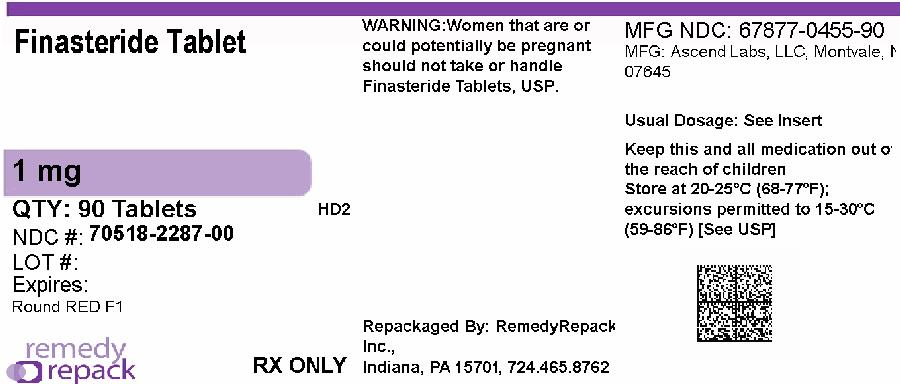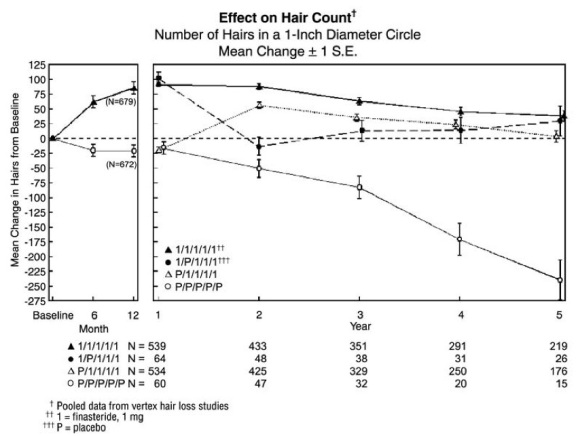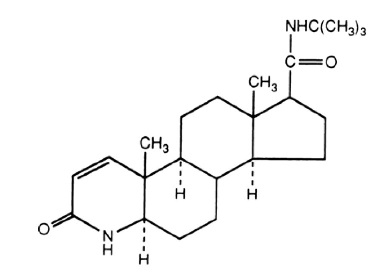 DRUG LABEL: Finasteride
NDC: 70518-2287 | Form: TABLET, COATED
Manufacturer: REMEDYREPACK INC.
Category: prescription | Type: HUMAN PRESCRIPTION DRUG LABEL
Date: 20260203

ACTIVE INGREDIENTS: FINASTERIDE 1 mg/1 1
INACTIVE INGREDIENTS: LACTOSE MONOHYDRATE; MICROCRYSTALLINE CELLULOSE; STARCH, CORN; SODIUM STARCH GLYCOLATE TYPE A POTATO; MAGNESIUM STEARATE; LAUROYL PEG-32 GLYCERIDES; HYPROMELLOSE 2910 (6 MPA.S); TITANIUM DIOXIDE; POLYETHYLENE GLYCOL 6000; FERRIC OXIDE RED; FERRIC OXIDE YELLOW

HIGHLIGHTS OF PRESCRIBING INFORMATION

These highlights do not include all the information needed to use FINASTERIDE TABLETS safely and effectively. See full prescribing information for FINASTERIDE TABLETS.
FINASTERIDE tablets for oral use
Initial U.S. Approval: 1992

1 INDICATIONS AND USAGE

- Finasteride tablets is a 5α-reductase inhibitor indicated for the treatment of male pattern hair loss (androgenetic alopecia) in MEN ONLY (1).
- Finasteride tablets is not indicated for use in women (1, 4, 5.1).

2 DOSAGE AND ADMINISTRATION

- Finasteride tablets may be administered with or without meals (2).
- One tablet (1 mg) taken once daily (2).
- In general, daily use for three months or more is necessary before benefit is observed (2).

3 DOSAGE FORMS AND STRENGTHS

1 mg tablets (3).

4 CONTRAINDICATIONS

- Pregnancy (4, 5.1, 8.1, 16).
- Hypersensitivity to any components of this product (4).

5 WARNINGS AND PRECAUTIONS

- Finasteride tablets is not indicated for use in women or pediatric patients (5.1, 5.4).
- Women should not handle crushed or broken finasteride tablets when they are pregnant or may potentially be pregnant due to potential risk to a male fetus (5.1, 8.1, 16).
- Finasteride tablets causes a decrease in serum PSA levels. Any confirmed increase in PSA while on finasteride tablets may signal the presence of prostate cancer and should be evaluated, even if those values are still within the normal range for men not taking a 5α-reductase inhibitor (5.2).
- 5α-reductase inhibitors may increase the risk of high - grade prostate cancer (5.3, 6.1).

6 ADVERSE REACTIONS

The most common adverse reactions, reported in ≥1% of patients treated with finasteride tablets and greater than in patients treated with placebo are: decreased libido, erectile dysfunction and ejaculation disorder (6.1).
To report SUSPECTED ADVERSE REACTIONS, contact Ascend Laboratories, LLC at 1-877-272-7901 or FDA at 1-800-FDA-1088 or www.fda.gov/medwatch.

FULL PRESCRIBING INFORMATION

1 INDICATIONS AND USAGE

Finasteride tablets is indicated for the treatment of male pattern hair loss (androgenetic alopecia) in MEN ONLY.

Efficacy in bitemporal recession has not been established.

Finasteride tablets is not indicated for use in women.

2 DOSAGE AND ADMINISTRATION

Finasteride tablets may be administered with or without meals.

The recommended dose of finasteride tablets, USP 1 mg is one tablet (1 mg) taken once daily.

In general, daily use for three months or more is necessary before benefit is observed. Continued use is recommended to sustain benefit, which should be re-evaluated periodically. Withdrawal of treatment leads to reversal of effect within 12 months.

3 DOSAGE FORMS AND STRENGTHS

Finasteride tablets (1 mg) are reddish brown colored, 7 mm round, biconvex, film coated tablets, marked “F1” on one side and plain on other side.

4 CONTRAINDICATIONS

Finasteride tablets is contraindicated in the following:

- Pregnancy. Finasteride use is contraindicated in women when they are or may potentially be pregnant. Because of the ability of Type II 5α-reductase inhibitors to inhibit the conversion of testosterone to 5α-dihydrotestosterone (DHT), finasteride may cause abnormalities of the external genitalia of a male fetus of a pregnant woman who receives finasteride. If this drug is used during pregnancy, or if pregnancy occurs while taking this drug, the pregnant woman should be apprised of the potential hazard to the male fetus. [ See Warnings and Precautions (5.1), Use in Specific Populations (8.1), How Supplied / Storage and Handling (16) and Patient Counseling Information (17).] In female rats, low doses of finasteride administered during pregnancy have produced abnormalities of the external genitalia in male offspring.
- Hypersensitivity to any component of this medication.

5 WARNINGS AND PRECAUTIONS

5.1 Exposure of Women — Risk to Male Fetus

Finasteride tablets is not indicated for use in women. Women should not handle crushed or broken finasteride tablets when they are pregnant or may potentially be pregnant because of the possibility of absorption of finasteride and the subsequent potential risk to a male fetus. Finasteride tablets are coated and will prevent contact with the active ingredient during normal handling, provided that the tablets have not been broken or crushed. [See Indications and Usage (1), Contraindications (4), Use in Specific Populations (8.1), How Supplied / Storage and Handling (16) and Patient Counseling Information (17).]

5.2 Effects on Prostate Specific Antigen (PSA)

In clinical studies with finasteride tablets (finasteride, 1 mg) in men 18 to 41 years of age, the mean value of serum prostate specific antigen (PSA) decreased from 0.7 ng/mL at baseline to 0.5 ng/mL at Month 12. Further, in clinical studies with finasteride tablets (finasteride, 5 mg) when used in older men who have benign prostatic hyperplasia (BPH), PSA levels are decreased by approximately 50%. Other studies with finasteride tablets showed it may also cause decreases in serum PSA in the presence of prostate cancer. These findings should be taken into account for proper interpretation of serum PSA when evaluating men treated with finasteride. Any confirmed increase from the lowest PSA value while on finasteride tablets may signal the presence of prostate cancer and should be evaluated, even if PSA levels are still within the normal range for men not taking a 5α-reductase inhibitor. Non-compliance to therapy with finasteride tablets may also affect PSA test results.

5.3 Increased Risk of High-Grade Prostate Cancer with 5α-Reductase Inhibitors

Men aged 55 and over with a normal digital rectal examination and PSA ≤3.0 ng/mL at baseline taking finasteride 5 mg/day (5 times the dose of finasteride tablets) in the 7-year Prostate Cancer Prevention Trial (PCPT) had an increased risk of Gleason score 8 to 10 prostate cancer (finasteride 1.8% vs placebo 1.1%). [ See Adverse Reactions (6.1).] Similar results were observed in a 4-year placebo-controlled clinical trial with another 5α-reductase inhibitor (dutasteride, AVODART) (1% dutasteride vs 0.5% placebo). 5α- reductase inhibitors may increase the risk of development of high-grade prostate cancer. Whether the effect of 5α-reductase inhibitors to reduce prostate volume, or study-related factors, impacted the results of these studies has not been established.

5.4 Pediatric Patients

Finasteride tablets is not indicated for use in pediatric patients [see Use in Specific Populations (8.4)].

6 ADVERSE REACTIONS

6.1 Clinical Trials Experience

Because clinical trials are conducted under widely varying conditions, adverse reaction rates observed in the clinical trials of a drug cannot be directly compared to rates in the clinical trials of another drug and may not reflect the rates observed in clinical practice.

Clinical Studies for finasteride tablets 1 mg in the Treatment of Male Pattern Hair Loss

In three controlled clinical trials for finasteride tablets of 12-month duration, 1.4% of patients taking finasteride tablets (n=945) were discontinued due to adverse experiences that were considered to be possibly, probably or definitely drug-related (1.6% for placebo; n=934).

Clinical adverse experiences that were reported as possibly, probably or definitely drug-related in >1% of patients treated with finasteride tablets or placebo are presented in Table 1.

TABLE 1: Drug-Related Adverse Experiences for Finasteride tablets 1 mg (finasteride 1 mg) in Year 1 (%)
MALE PATTERN HAIR LOSS
 | Finasteride N=945 | Placebo N=934
Decreased Libido | 1.8 | 1.3
Erectile Dysfunction | 1.3 | 0.7
Ejaculation Disorder (Decreased Volume of Ejaculate) | 1.2 (0.8) | 0.7 (0.4)
Discontinuation due to drug-related sexual adverse experiences | 1.2 | 0.9

Integrated analysis of clinical adverse experiences showed that during treatment with finasteride tablets, 36 (3.8%) of 945 men had reported one or more of these adverse experiences as compared to 20 (2.1%) of 934 men treated with placebo (p=0.04). Resolution occurred in men who discontinued therapy with finasteride tablets due to these side effects and in most of those who continued therapy. The incidence of each of the above adverse experiences decreased to <0.3% by the fifth year of treatment with finasteride tablets.

In a study of finasteride 1 mg daily in healthy men, a median decrease in ejaculate volume of 0.3 mL (-11%) compared with 0.2 mL (-8%) for placebo was observed after 48 weeks of treatment. Two other studies showed that finasteride at 5 times the dosage of finasteride tablets (5 mg daily) produced significant median decreases of approximately 0.5 mL (-25%) compared to placebo in ejaculate volume, but this was reversible after discontinuation of treatment.

In the�clinical studies with finasteride tablets, the incidences for breast tenderness and enlargement, hypersensitivity reactions, and testicular pain in finasteride-treated patients were not different from those in patients treated with placebo .

Controlled Clinical Trials and Long-Term Open Extension Studies for finasteride tablets (finasteride 5 mg) and AVODART (dutasteride) in the Treatment of Benign Prostatic Hyperplasia

In the finasteride tablets 5 mg Long-Term Efficacy and Safety Study (PLESS), a 4-year controlled clinical study, 3,040 patients between the ages of 45 and 78 with symptomatic BPH and an enlarged prostate were evaluated for safety over a period of 4 years (1,524 on finasteride tablets 5 mg/day and 1,516 on placebo). 3.7% (57 patients) treated with finasteride tablets 5 mg and 2.1% (32 patients) treated with placebo discontinued therapy as a result of adverse reactions related to sexual function, which are the most frequently reported adverse reactions.

Table 2 presents the only clinical adverse reactions considered possibly, probably or definitely drug related by the investigator, for which the incidence on finasteride tablets 5 mg was >1% and greater than placebo over the 4 years of the study. In years 2 to 4 of the study, there was no significant difference between treatment groups in the incidences of impotence, decreased libido and ejaculation disorder.

TABLE 2: Drug-Related Adverse Experiences for finasteride tablets 5 mgBENIGN PROSTATIC HYPERPLASIA
 | Year 1 (%) |  | Years 2, 3 and 4* (%)
 | Finasteride 5 mg | Placebo | Finasteride 5 mg | Placebo
Impotence | 8.1 | 3.7 | 5.1 | 5.1
Decreased Libido | 6.4 | 3.4 | 2.6 | 2.6
Decreased Volume of Ejaculate | 3.7 | 0.8 | 1.5 | 0.5
Ejaculation Disorder | 0.8 | 0.1 | 0.2 | 0.1
Breast Enlargement | 0.5 | 0.1 | 1.8 | 1.1
Breast Tenderness | 0.4 | 0.1 | 0.7 | 0.3
Rash | 0.5 | 0.2 | 0.5 | 0.1

*Combined Years 2 to 4

N = 1,524 and 1,516, finasteride vs placebo, respectively

The adverse experience profiles in the 1-year, placebo-controlled, Phase III BPH studies and the 5-year open extensions with finasteride tablets 5 mg and PLESS were similar.

There is no evidence of increased sexual adverse experiences with increased duration of treatment with finasteride tablets 5 mg. New reports of drug-related sexual adverse experiences decreased with duration of therapy.

During the 4- to 6-year placebo- and comparator-controlled Medical Therapy of Prostatic Symptoms (MTOPS) study that enrolled 3,047 men, there were 4 cases of breast cancer in men treated with finasteride tablets 5 mg but no cases in men not treated with finasteride tablets 5 mg. During the 4-year placebo-controlled PLESS study that enrolled 3,040 men, there were 2 cases of breast cancer in placebo-treated men, but no cases were reported in men treated with finasteride tablets 5 mg.

During the 7-year placebo-controlled Prostate Cancer Prevention Trial (PCPT) that enrolled 18,882 men, there was 1 case of breast cancer in men treated with finasteride tablets, and 1 case of breast cancer in men treated with placebo. The relationship between long-term use of finasteride and male breast neoplasia is currently unknown.

The PCPT trial was a 7-year randomized, double-blind, placebo-controlled trial that enrolled 18,882 healthy men ≥55 years of age with a normal digital rectal examination and a PSA ≤3.0 ng/mL. Men received either finasteride tablets 5 mg (finasteride 5 mg) or placebo daily. Patients were evaluated annually with PSA and digital rectal exams. Biopsies were performed for elevated PSA, an abnormal digital rectal exam, or the end of study. The incidence of Gleason score 8 to 10 prostate cancer was higher in men treated with finasteride (1.8%) than in those treated with placebo (1.1%). In a 4-year placebo-controlled clinical trial with another 5α-reductase inhibitor [AVODART (dutasteride)], similar results for Gleason score 8 to 10 prostate cancer were observed (1% dutasteride vs 0.5% placebo). The clinical significance of these findings with respect to use of finasteride tablets by men is unknown.

No clinical benefit has been demonstrated in patients with prostate cancer treated with finasteride tablets. Finasteride tablets is not approved to reduce the risk of developing prostate cancer.

Sexual Function Questionnaire
A sexual function questionnaire was self-administered by patients participating in the two vertex baldness trials to detect more subtle changes in sexual function. At Month 12, statistically significant differences in favor of placebo were found in 3 of 4 domains (sexual interest, erections, and perception of sexual problems). However, no significant difference was seen in the question on overall satisfaction with sex life.
In one of the two vertex baldness studies, patients were questioned on non-scalp body hair growth. Finasteride tablets did not appear to affect non-scalp body hair.

6.2 Postmarketing Experience

The following adverse reactions have been identified during post approval use of finasteride tablets. Because these reactions are reported voluntarily from a population of uncertain size, it is not always possible to reliably estimate their frequency or establish a causal relationship to drug exposure:

Hypersensitivity Reaction:hypersensitivity reactions such as rash, pruritus, urticaria, and angioedema (including swelling of the lips, tongue, throat, and face);

Reproductive System:sexual dysfunction that continued after discontinuation of treatment, including erectile dysfunction, libido disorders, ejaculation disorders, and orgasm disorders; male infertility and/or poor seminal quality (normalization or improvement of seminal quality has been reported after discontinuation of finasteride); testicular pain; hematospermia.

Neoplasms:male breast cancer;

Breast disorders:breast tenderness and enlargement;

Nervous System/Psychiatric:depression, suicidal ideation and behavior.

7 DRUG INTERACTIONS

7.1 Cytochrome P450-Linked Drug Metabolizing Enzyme System

No drug interactions of clinical importance have been identified. Finasteride does not appear to affect the cytochrome P450-linked drug-metabolizing enzyme system. Compounds that have been tested in man include antipyrine, digoxin, propranolol, theophylline, and warfarin and no clinically meaningful interactions were found.

7.2 Other Concomitant Therapy

Although specific interaction studies were not performed, finasteride doses of 1 mg or more were concomitantly used in clinical studies with acetaminophen, acetylsalicylic acid, α-blockers, analgesics, angiotensin-converting enzyme (ACE) inhibitors, anticonvulsants, benzodiazepines, beta blockers, calcium-channel blockers, cardiac nitrates, diuretics, H2 antagonists, HMG-CoA reductase inhibitors, prostaglandin synthetase inhibitors (also referred to as NSAIDs), and quinolone anti-infectives without evidence of clinically significant adverse interactions.

8 USE IN SPECIFIC POPULATIONS

8.1 Pregnancy

Pregnancy Category X [ see Contraindications (4)] .

Finasteride tablets is contraindicated for use in women who are or may become pregnant. Finasteride tablets is a Type II 5α-reductase inhibitor that prevents conversion of testosterone to 5α-dihydrotestosterone (DHT), a hormone necessary for normal development of male genitalia. In animal studies, finasteride caused abnormal development of external genitalia in male fetuses. If this drug is used during pregnancy, or if the patient becomes pregnant while taking this drug, the patient should be apprised of the potential hazard to the male fetus.

Abnormal male genital development is an expected consequence when conversion of testosterone to 5α- dihydrotestosterone (DHT) is inhibited by 5α-reductase inhibitors. These outcomes are similar to those reported in male infants with genetic 5α-reductase deficiency. Women could be exposed to finasteride through contact with crushed or broken finasteride tablets or semen from a male partner taking finasteride tablets. With regard to finasteride exposure through the skin, finasteride tablets are coated and will prevent skin contact with finasteride during normal handling if the tablets have not been crushed or broken. Women who are pregnant or may become pregnant should not handle crushed or broken finasteride tablets because of possible exposure of a male fetus. If a pregnant woman comes in contact with crushed or broken finasteride tablets, the contact area should be washed immediately with soap and water. With regard to potential finasteride exposure through semen, a study has been conducted in men receiving finasteride tablets 1 mg/day that measured finasteride concentrations in semen

[ see Clinical Pharmacology (12.3)].

In an embryo-fetal development study, pregnant rats received finasteride during the period of major organogenesis (gestation days 6 to 17). At maternal doses of oral finasteride approximately 1 to 684 times the recommended human dose (RHD) of 1 mg/day (based on AUC at animal doses of 0.1 to 100 mg/kg/day) there was a dose-dependent increase in hypospadias that occurred in 3.6 to 100% of male offspring. Exposure multiples were estimated using data from nonpregnant rats. Days 16 to 17 of gestation is a critical period in male fetal rats for differentiation of the external genitalia. At oral maternal doses approximately 0.2 times the RHD (based on AUC at animal dose of 0.03 mg/kg/day), male offspring had decreased prostatic and seminal vesicular weights, delayed preputial separation and transient nipple development. Decreased anogenital distance occurred in male offspring of pregnant rats that received approximately 0.02 times the RHD (based on AUC at animal dose of 0.003 mg/kg/day). No abnormalities were observed in female offspring exposed to any dose of finasteride in utero.

No developmental abnormalities were observed in the offspring of untreated females mated with finasteride-treated male rats that received approximately 488 times the RHD (based on AUC at animal dose of 80 mg/kg/day). Slightly decreased fertility was observed in male offspring after administration of about 20 times the RHD (based on AUC at animal dose of 3 mg/kg/day) to female rats during late gestation and lactation. No effects on fertility were seen in female offspring under these conditions.

No evidence of male external genital malformations or other abnormalities were observed in rabbit fetuses exposed to finasteride during the period of major organogenesis (gestation days 6 to 18) at maternal doses up to 100 mg/kg/day (finasteride exposure levels were not measured in rabbits). However, this study may not have included the critical period for finasteride effects on development of male external genitalia in the rabbit.

The fetal effects of maternal finasteride exposure during the period of embryonic and fetal development were evaluated in the rhesus monkey (gestation days 20 to 100), in a species and development period more predictive of specific effects in humans than the studies in rats and rabbits. Intravenous administration of finasteride to pregnant monkeys at doses as high as 800 ng/day (estimated maximal blood concentration of 1.86 ng/mL or about 930 times the highest estimated exposure of pregnant women to finasteride from semen of men taking 1 mg/day) resulted in no abnormalities in male fetuses. In confirmation of the relevance of the rhesus model for human fetal development, oral administration of a dose of finasteride (2 mg/kg/day or approximately 120,000 times the highest estimated blood levels of finasteride from semen of men taking 1 mg/day) to pregnant monkeys resulted in external genital abnormalities in male fetuses. No other abnormalities were observed in male fetuses and no finasteride- related abnormalities were observed in female fetuses at any dose.

8.3 Nursing Mothers

Finasteride tablets is not indicated for use in women.
It is not known whether finasteride is excreted in human milk.

8.4 Pediatric Use

Finasteride tablets is not indicated for use in pediatric patients.
Safety and effectiveness in pediatric patients have not been established.

8.5 Geriatric Use

Clinical efficacy studies with finasteride tablets did not include subjects aged 65 and over. Based on the pharmacokinetics of finasteride 5 mg, no dosage adjustment is necessary in the elderly for finasteride tablets [see Clinical Pharmacology (12.3)]. However the efficacy of finasteride tablets in the elderly has not been established.

8.6 Hepatic Impairment

Caution should be exercised in the administration of finasteride tablets in those patients with liver function abnormalities, as finasteride is metabolized extensively in the liver [ see Clinical Pharmacology (12.3)] .

8.7 Renal Impairment

No dosage adjustment is necessary in patients with renal impairment [ see Clinical Pharmacology (12.3)] .

10 OVERDOSAGE

In clinical studies, single doses of finasteride up to 400 mg and multiple doses of finasteride up to 80 mg/day for three months did not result in adverse reactions. Until further experience is obtained, no specific treatment for an overdose with finasteride can be recommended.

Significant lethality was observed in male and female mice at single oral doses of 1,500 mg/m^2(500 mg/kg) and in female and male rats at single oral doses of 2,360 mg/m^2(400 mg/kg) and 5,900 mg/m^2(1,000 mg/kg), respectively.

11 DESCRIPTION

Finasteride tablets, USP contain finasteride as the active ingredient. Finasteride, a synthetic 4-azasteroid compound, is a specific inhibitor of steroid Type II 5α-reductase, an intracellular enzyme that converts the androgen testosterone into 5α-dihydrotestosterone (DHT).

The chemical name of finasteride is N-tert-Butyl-3-oxo-4-aza-5α-androst-1-ene-17β-carboxamide. The empirical formula of finasteride is C23H36N2O2 and its molecular weight is 372.55. Its structural formula is:

Finasteride is a white crystalline powder with a melting point near 250°C. It is freely soluble in chloroform and in lower alcohol solvents but is practically insoluble in water.

Finasteride Tablets, USP are film-coated tablets for oral administration. Each tablet contains 1 mg of finasteride and the following inactive ingredients: hypromellose, iron oxide red, iron oxide yellow, lactose monohydrate, lauroylmacrogol 32 glycerides, magnesium stearate, microcrystalline cellulose, polyethylene glycol, pregelatinized starch, sodium starch glycolate, and titanium dioxide.

12 CLINICAL PHARMACOLOGY

12.1 Mechanism of Action

Finasteride is a competitive and specific inhibitor of Type II 5α-reductase, an intracellular enzyme that converts the androgen testosterone into DHT. Two distinct isozymes are found in mice, rats, monkeys, and humans: Type I and II. Each of these isozymes is differentially expressed in tissues and developmental stages. In humans, Type I 5 α-reductase is predominant in the sebaceous glands of most regions of skin, including scalp, and liver. Type I 5 α-reductase is responsible for approximately one-third of circulating DHT. The Type II 5 α-reductase isozyme is primarily found in prostate, seminal vesicles, epididymides, and hair follicles as well as liver, and is responsible for two-thirds of circulating DHT.

In humans, the mechanism of action of finasteride is based on its preferential inhibition of the Type II isozyme. Using native tissues (scalp and prostate), in vitrobinding studies examining the potential of finasteride to inhibit either isozyme revealed a 100-fold selectivity for the human Type II 5 α-reductase over Type I isozyme (IC50=500 and 4.2 nM for Type I and II, respectively). For both isozymes, the inhibition by finasteride is accompanied by reduction of the inhibitor to dihydrofinasteride and adduct formation with NADP+. The turnover for the enzyme complex is slow (t1/2approximately 30 days for the Type II enzyme complex and 14 days for the Type I complex). Inhibition of Type II 5 α-reductase blocks the peripheral conversion of testosterone to DHT, resulting in significant decreases in serum and tissue DHT concentrations.

In men with male pattern hair loss (androgenetic alopecia), the balding scalp contains miniaturized hair follicles and increased amounts of DHT compared with hairy scalp. Administration of finasteride decreases scalp and serum DHT concentrations in these men. The relative contributions of these reductions to the treatment effect of finasteride have not been defined. By this mechanism, finasteride appears to interrupt a key factor in the development of androgenetic alopecia in those patients genetically predisposed.

12.2 Pharmacodynamics

Finasteride produces a rapid reduction in serum DHT concentration, reaching 65% suppression within 24 hours of oral dosing with a 1-mg tablet. Mean circulating levels of testosterone and estradiol were increased by approximately 15% as compared to baseline, but these remained within the physiologic range.

Finasteride has no affinity for the androgen receptor and has no androgenic, antiandrogenic, estrogenic, antiestrogenic, or progestational effects. The relationship between these pharmacodynamic activities and the mechanisms(s) by which finasteride tablets exerts its clinical effect is unknown. In studies with finasteride, no clinically meaningful changes in luteinizing hormone (LH), follicle-stimulating hormone (FSH) or prolactin were detected. In healthy volunteers, treatment with finasteride did not alter the response of LH and FSH to gonadotropin-releasing hormone indicating that the hypothalamic-pituitary-testicular axis was not affected. Finasteride had no effect on circulating levels of cortisol, thyroid-stimulating hormone, or thyroxine, nor did it affect the plasma lipid profile (e.g., total cholesterol, low-density lipoproteins, high-density lipoproteins and triglycerides) or bone mineral density.

12.3 Pharmacokinetics

Absorption

In a study in 15 healthy young male subjects, the mean bioavailability of finasteride 1-mg tablets was 65% (range 26 to 170%), based on the ratio of area under the curve (AUC) relative to an intravenous (IV) reference dose. At steady state following dosing with 1 mg/day (n=12), maximum finasteride plasma concentration averaged 9.2 ng/mL (range, 4.9 to 13.7 ng/mL) and was reached 1 to 2 hours postdose; AUC(0-24 hr)was 53 ng•hr/mL (range, 20 to 154 ng•hr/mL). Bioavailability of finasteride was not affected by food.

Distribution

Mean steady-state volume of distribution was 76 liters (range, 44 to 96 liters; n=15). Approximately 90% of circulating finasteride is bound to plasma proteins. There is a slow accumulation phase for finasteride after multiple dosing.

Finasteride has been found to cross the blood-brain barrier.

Semen levels have been measured in 35 men taking finasteride 1 mg/day for 6 weeks. In 60% (21 of 35) of the samples, finasteride levels were undetectable (<0.2 ng/mL). The mean finasteride level was 0.26 ng/mL and the highest level measured was 1.52 ng/mL. Using the highest semen level measured and assuming 100% absorption from a 5-mL ejaculate per day, human exposure through vaginal absorption would be up to 7.6 ng per day, which is 650-fold less than the dose of finasteride (5 µg) that had no effect on circulating DHT levels in men. [See Use in Specific Populations (8.1). ]

Metabolism

Finasteride is extensively metabolized in the liver, primarily via the cytochrome P450 3A4 enzyme subfamily. Two metabolites, the t-butyl side chain monohydroxylated and monocarboxylic acid metabolites, have been identified that possess no more than 20% of the 5α-reductase inhibitory activity of finasteride.

Excretion

Following intravenous infusion in healthy young subjects (n=15), mean plasma clearance of finasteride was 165 mL/min (range, 70 to 279 mL/min). Mean terminal half-life in plasma was 4.5 hours (range, 3.3 to 13.4 hours; n=12). Following an oral dose of^14C-finasteride in man (n=6), a mean of 39% (range, 32 to 46%) of the dose was excreted in the urine in the form of metabolites; 57% (range, 51 to 64%) was excreted in the feces.

Mean terminal half-life is approximately 5 to 6 hours in men 18 to 60 years of age and 8 hours in men more than 70 years of age.

TABLE 3: Mean (SD) Pharmacokinetic Parameters in Healthy Men (ages 18 to 26)
 | Mean (±SD) n=15
Bioavailability | 65% (26 to 170%)*
Clearance (mL/min) | 165 (55)
Volume of Distribution (L) | 76 (14)

*Range

TABLE 4: Mean (SD) Noncompartmental Pharmacokinetic Parameters After Multiple Doses of 1 mg/day in Healthy Men (ages 19 to 42)
 | Mean (±SD) (n=12)
AUC (ng.hr/mL) | 53 (33.8)
Peak Concentration (ng/mL) | 9.2 (2.6)
Time to Peak (hours) | 1.3 (0.5)
Half-Life (hours)* | 4.5 (1.6)

*First-dose values; all other parameters are last-dose values

Renal Impairment

No dosage adjustment is necessary in patients with renal impairment. In patients with chronic renal impairment, with creatinine clearances ranging from 9.0 to 55 mL/min, AUC, maximum plasma concentration, half-life, and protein binding after a single dose of^14C-finasteride were similar to those obtained in healthy volunteers. Urinary excretion of metabolites was decreased in patients with renal impairment. This decrease was associated with an increase in fecal excretion of metabolites. Plasma concentrations of metabolites were significantly higher in patients with renal impairment (based on a 60% increase in total radioactivity AUC). However, finasteride has been tolerated in men with normal renal function receiving up to 80 mg/day for 12 weeks where exposure of these patients to metabolites would presumably be much greater.

Hepatic Impairment

The effect of hepatic impairment on finasteride pharmacokinetics has not been studied. Caution should be used in the administration of finasteride tablets in patients with liver function abnormalities, as finasteride is metabolized extensively in the liver.

13 NONCLINICAL TOXICOLOGY

13.1 Carcinogenesis, Mutagenesis, Impairment of Fertility

No evidence of a tumorigenic effect was observed in a 24-month study in Sprague-Dawley rats receiving doses of finasteride up to 160 mg/kg/day in males and 320 mg/kg/day in females. These doses produced respective systemic exposure in rats of 888 and 2,192 times those observed in man receiving the recommended human dose of 1 mg/day. All exposure calculations were based on calculated AUC(0-24 hr)for animals and mean AUC(0-24 hr) for man (0.05 µg•hr/mL).

In a 19-month carcinogenicity study in CD-1 mice, a statistically significant (p <0.05) increase in the incidence of testicular Leydig cell adenomas was observed at 1,824 times the human exposure (250 mg/kg/day). In mice at 184 times the human exposure, estimated (25 mg/kg/day) and in rats at 312 times the human exposure (>40 mg/kg/day) an increase in the incidence of Leydig cell hyperplasia was observed. A positive correlation between the proliferative changes in the Leydig cells and an increase in serum LH levels (2- to 3-fold above control) has been demonstrated in both rodent species treated with high doses of finasteride. No drug-related Leydig cell changes were seen in either rats or dogs treated with finasteride for 1 year at 240 and 2,800 times (20 mg/kg/day and 45 mg/kg/day, respectively), or in mice treated for 19 months at 18.4 times the human exposure, estimated (2.5 mg/kg/day).

No evidence of mutagenicity was observed in an in vitrobacterial mutagenesis assay, a mammalian cell mutagenesis assay, or in an in vitroalkaline elution assay. In an in vitrochromosome aberration assay, using Chinese hamster ovary cells, there was a slight increase in chromosome aberrations. In an in vivochromosome aberration assay in mice, no treatment-related increase in chromosome aberration was observed with finasteride at the maximum tolerated dose of 250 mg/kg/day (1,824 times the human exposure) as determined in the carcinogenicity studies. In sexually mature male rabbits treated with finasteride at 4,344 times the human exposure (80 mg/kg/day) for up to 12 weeks, no effect on fertility, sperm count, or ejaculate volume was seen. In sexually mature male rats treated with 488 times the human exposure (80 mg/kg/day), there were no significant effects on fertility after 6 or 12 weeks of treatment; however, when treatment was continued for up to 24 or 30 weeks, there was an apparent decrease in fertility, fecundity, and an associated significant decrease in the weights of the seminal vesicles and prostate. All these effects were reversible within 6 weeks of discontinuation of treatment. No drug-related effect on testes or on mating performance has been seen in rats or rabbits. This decrease in fertility in finasteride-treated rats is secondary to its effect on accessory sex organs (prostate and seminal vesicles) resulting in failure to form a seminal plug. The seminal plug is essential for normal fertility in rats but is not relevant in man.

14 CLINICAL STUDIES

14.1 Studies in Men

The efficacy of finasteride tablets was demonstrated in men (88% Caucasian) with mild to moderate androgenetic alopecia (male pattern hair loss) between 18 and 41 years of age. In order to prevent seborrheic dermatitis which might confound the assessment of hair growth in these studies, all men, whether treated with finasteride or placebo, were instructed to use a specified, medicated, tar-based shampoo (Neutrogena T/Gel®Shampoo) during the first 2 years of the studies.

There were three double-blind, randomized, placebo-controlled studies of 12-month duration. The two primary endpoints were hair count and patient self-assessment; the two secondary endpoints were investigator assessment and ratings of photographs. In addition, information was collected regarding sexual function (based on a self-administered questionnaire) and non-scalp body hair growth. The three studies were conducted in 1,879 men with mild to moderate, but not complete, hair loss. Two of the studies enrolled men with predominantly mild to moderate vertex hair loss (n=1,553). The third enrolled men having mild to moderate hair loss in the anterior mid-scalp area with or without vertex balding (n=326).

Studies in Men with Vertex Baldness

Of the men who completed the first 12 months of the two vertex baldness trials, 1,215 elected to continue in double-blind, placebo-controlled, 12-month extension studies. There were 547 men receiving finasteride tablets for both the initial study and first extension periods (up to 2 years of treatment) and 60 men receiving placebo for the same periods. The extension studies were continued for 3 additional years, with 323 men on finasteride tablets and 23 on placebo entering the fifth year of the study.

In order to evaluate the effect of discontinuation of therapy, there were 65 men who received finasteride tablets for the initial 12 months followed by placebo in the first 12-month extension period. Some of these men continued in additional extension studies and were switched back to treatment with finasteride tablets, with 32 men entering the fifth year of the study. Lastly, there were 543 men who received placebo for the initial 12 months followed by finasteride tablets in the first 12-month extension period. Some of these men continued in additional extension studies receiving finasteride tablets, with 290 men entering the fifth year of the study (see Figure 1 below).

Hair counts were assessed by photographic enlargements of a representative area of active hair loss. In these two studies in men with vertex baldness, significant increases in hair count were demonstrated at 6 and 12 months in men treated with finasteride tablets, while significant hair loss from baseline was demonstrated in those treated with placebo. At 12 months there was a 107-hair difference from placebo (p<0.001, finasteride tablets [n=679] vs placebo [n=672]) within a 1-inch diameter circle (5.1 cm^2). Hair count was maintained in those men taking finasteride tablets for up to 2 years, resulting in a 138-hair difference between treatment groups (p<0.001, finasteride tablets [n=433] vs placebo [n=47]) within the same area. In men treated with finasteride tablets, the maximum improvement in hair count compared to baseline was achieved during the first 2 years. Although the initial improvement was followed by a slow decline, hair count was maintained above baseline throughout the 5 years of the studies. Furthermore, because the decline in the placebo group was more rapid, the difference between treatment groups also continued to increase throughout the studies, resulting in a 277-hair difference (p<0.001, finasteride tablets [n=219] vs placebo [n=15]) at 5 years (see Figure 1 below).

Patients who switched from placebo to finasteride tablets (n=425) had a decrease in hair count at the end of the initial 12-month placebo period, followed by an increase in hair count after 1 year of treatment with finasteride tablets. This increase in hair count was less (56 hairs above original baseline) than the increase (91 hairs above original baseline) observed after 1 year of treatment in men initially randomized to finasteride tablets. Although the increase in hair count, relative to when therapy was initiated, was comparable between these two groups, a higher absolute hair count was achieved in patients who were started on treatment with finasteride tablets in the initial study. This advantage was maintained through the remaining 3 years of the studies. A change of treatment from finasteride tablets to placebo (n=48) at the end of the initial 12 months resulted in reversal of the increase in hair count 12 months later, at 24 months (see Figure 1 below).

At 12 months, 58% of men in the placebo group had further hair loss (defined as any decrease in hair count from baseline), compared with 14% of men treated with finasteride tablets. In men treated for up to 2 years, 72% of men in the placebo group demonstrated hair loss, compared with 17% of men treated with finasteride tablets. At 5 years, 100% of men in the placebo group demonstrated hair loss, compared with 35% of men treated with finasteride tablets.

Figure 1

Patient self-assessment was obtained at each clinic visit from a self-administered questionnaire, which included questions on their perception of hair growth, hair loss, and appearance. This self-assessment demonstrated an increase in amount of hair, a decrease in hair loss, and improvement in appearance in men treated with finasteride tablets. Overall improvement compared with placebo was seen as early as 3 months (p<0.05), with improvement maintained over 5 years.

Investigator assessment was based on a 7-point scale evaluating increases or decreases in scalp hair at each patient visit. This assessment showed significantly greater increases in hair growth in men treated with finasteride tablets compared with placebo as early as 3 months (p<0.001). At 12 months, the investigators rated 65% of men treated with finasteride tablets as having increased hair growth compared with 37% in the placebo group. At 2 years, the investigators rated 80% of men treated with finasteride tablets as having increased hair growth compared with 47% of men treated with placebo. At 5 years, the investigators rated 77% of men treated with finasteride tablets as having increased hair growth, compared with 15% of men treated with placebo.

An independent panel rated standardized photographs of the head in a blinded fashion based on increases or decreases in scalp hair using the same 7-point scale as the investigator assessment. At 12 months, 48% of men treated with finasteride tablets had an increase as compared with 7% of men treated with placebo. At 2 years, an increase in hair growth was demonstrated in 66% of men treated with finasteride tablets, compared with 7% of men treated with placebo. At 5 years, 48% of men treated with finasteride tablets demonstrated an increase in hair growth, 42% were rated as having no change (no further visible progression of hair loss from baseline) and 10% were rated as having lost hair when compared to baseline. In comparison, 6% of men treated with placebo demonstrated an increase in hair growth, 19% were rated as having no change and 75% were rated as having lost hair when compared to baseline.

A 48-week, placebo-controlled study designed to assess by phototrichogram the effect of finasteride tablets on total and actively growing (anagen) scalp hairs in vertex baldness enrolled 212 men with androgenetic alopecia. At baseline and 48 weeks, total and anagen hair counts were obtained in a 1-cm^2target area of the scalp. Men treated with finasteride tablets showed increases from baseline in total and anagen hair counts of 7 hairs and 18 hairs, respectively, whereas men treated with placebo had decreases of 10 hairs and 9 hairs, respectively. These changes in hair counts resulted in a between-group difference of 17 hairs in total hair count (p<0.001) and 27 hairs in anagen hair count (p<0.001), and an improvement in the proportion of anagen hairs from 62% at baseline to 68% for men treated with finasteride tablets.

Study in Men with Hair Loss in the Anterior Mid-Scalp Area

A study of 12-month duration, designed to assess the efficacy of finasteride tablets in men with hair loss in the anterior mid-scalp area, also demonstrated significant increases in hair count compared with placebo. Increases in hair count were accompanied by improvements in patient self-assessment, investigator assessment, and ratings based on standardized photographs. Hair counts were obtained in the anterior mid-scalp area, and did not include the area of bitemporal recession or the anterior hairline.

Summary of Clinical Studies in Men

Clinical studies were conducted in men aged 18 to 41 with mild to moderate degrees of androgenetic alopecia. All men treated with finasteride tablets or placebo received a tar-based shampoo (Neutrogena T/Gel® Shampoo) during the first 2 years of the studies. Clinical improvement was seen as early as 3 months in the patients treated with finasteride tablets and led to a net increase in scalp hair count and hair regrowth. In clinical studies for up to 5 years, treatment with finasteride tablets slowed the further progression of hair loss observed in the placebo group. In general, the difference between treatment groups continued to increase throughout the 5 years of the studies.

Ethnic Analysis of Clinical Data from Men

In a combined analysis of the two studies on vertex baldness, mean hair count changes from baseline were 91 vs -19 hairs (Finasteride tablets vs placebo) among Caucasians (n=1,185), 49 vs -27 hairs among Blacks (n=84), 53 vs -38 hairs among Asians (n=17), 67 vs 5 hairs among Hispanics (n=45) and 67 vs -15 hairs among other ethnic groups (n=20). Patient self-assessment showed improvement across racial groups with finasteride tablets treatment, except for satisfaction of the frontal hairline and vertex in Black men, who were satisfied overall.

14.2 Study in Women

In a study involving 137 postmenopausal women with androgenetic alopecia who were treated with finasteride tablets (n=67) or placebo (n=70) for 12 months, effectiveness could not be demonstrated. There was no improvement in hair counts, patient self-assessment, investigator assessment, or ratings of standardized photographs in the women treated with finasteride tablets when compared with the placebo group [see Indications and Usage (1)].

16 HOW SUPPLIED/STORAGE AND HANDLING

Finasteride tablets, USP 1 mg are available as reddish brown colored, 7 mm round, biconvex, film coated tablets, marked “F1” on one side and plain on other side. They are supplied as follows:

NDC: 70518-2287-00

NDC: 70518-2287-01

NDC: 70518-2287-02

PACKAGING: 90 in 1 BOTTLE PLASTIC

PACKAGING: 30 in 1 BOTTLE PLASTIC

PACKAGING: 30 in 1 BLISTER PACK

Storage and Handling

Store at 20º to 25ºC (68º to 77ºF) [See USP Controlled Room Temperature]. Preserve in a tight, light-resistant container.

Women should not handle crushed or broken finasteride tablets when they are pregnant or may potentially be pregnant because of the possibility of absorption of finasteride and the subsequent potential risk to a male fetus. Finasteride tablets, USP 1 mg are coated and will prevent contact with the active ingredient during normal handling, provided that the tablets are not broken or crushed [ see Warnings and Precautions (5.1), Use in Specific Populations (8.1)and Patient Counseling Information (17)] .

Repackaged and Distributed By:

Remedy Repack, Inc.

625 Kolter Dr. Suite #4 Indiana, PA 1-724-465-8762

17 PATIENT COUNSELING INFORMATION

Advise the patient to read the FDA-approved patient labeling (Patient Information).

Exposure of Women — Risk to Male Fetus

Physicians should inform patients that women who are pregnant or may potentially be pregnant should not handle crushed or broken finasteride tablets because of the possibility of absorption of finasteride and the subsequent potential risk to a male fetus. Finasteride tablets are coated and will prevent contact with the active ingredient during normal handling, provided that the tablets have not been broken or crushed. If a woman who is pregnant or may potentially be pregnant comes in contact with crushed or broken finasteride tablets, the contact area should be washed immediately with soap and water [see Contraindications (4), Warnings and Precautions (5.1), Use in Specific Populations (8.1)and How Supplied/Storage and Handling (16)].

Increased Risk of High-Grade Prostate Cancer

Patients should be informed that there was an increase in high-grade prostate cancer in men treated with 5α-reductase inhibitors indicated for BPH treatment, compared to those treated with placebo in studies looking at the use of these drugs to prevent prostate cancer [see Warnings and Precautions (5.3)and Adverse Reactions (6.1)].

Sexual Adverse events
Physicians should inform the patients that finasteride tablets may cause symptoms of sexual dysfunction such as decreased libido, erectile dysfunction, and ejaculation disorder, including decreased ejaculate volume.

Additional Instructions

Physicians should instruct their patients to promptly report any changes in their breasts such as lumps, pain or nipple discharge. Breast changes including breast enlargement, tenderness and neoplasm have been reported [see Adverse Reactions (6.1)].

Physicians should instruct their patients to read the patient package insert before starting therapy with finasteride tablets and to read it again each time the prescription is renewed so that they are aware of current information for patients regarding finasteride tablets.

The trademarks depicted herein are owned by their respective companies.

For Patient Information, please visit:
http://www.ascendlaboratories.com/pti/finasteridetab1mg.pdf

Repackaged By / Distributed By: RemedyRepack Inc.

625 Kolter Drive, Indiana, PA 15701

(724) 465-8762

Patient Information

Finasteride Tablets, USP

(fin NAH steh ride)

Finasteride Tablets, USP is for use by MEN ONLYand should NOTbe used by women or children.

Read this Patient Information before you start taking finasteride tablets, USP and each time you get a refill. There may be new information. This information does not take the place of talking with your healthcare provider about your medical condition or treatment.

What isfinasteride tablets, USP?

Finasteride tablets, USP is a prescription medicine used for the treatment of male pattern hair loss (androgenetic alopecia).

It is not known if Finasteride tablets, USP works for a receding hairline on either side of and above your forehead (temporal area).

Finasteride tablets, USPis not for use by women and children.

Who should not takefinasteride tablets, USP?

Do not takefinasteride tablets, USPif you:

- are pregnant or may become pregnant. Finasteride Tablets, USP 1 mg may harm your unborn baby.

o Finasteride tablets, USP are coated and will prevent contact with the medicine during handling, as long as the tablets are not broken or crushed. Females who are pregnant or who may become pregnant should not come in contact with broken or crushed Finasteride tablets, USP. If a pregnant woman comes in contact with crushed or broken Finasteride tablets, USP, wash the contact area right away with soap and water. If a woman who is pregnant comes into contact with the active ingredient in Finasteride tablets, USP, a healthcare provider should be consulted.

o If a woman who is pregnant with a male baby swallows or comes in contact with the medicine in finasteride tablets, USP, the male baby may be born with sex organs that are not normal.

· are allergic to any of the ingredients in finasteride tablets, USP. See the end of this leaflet for a complete list of ingredients in finasteride tablets, USP.

What should I tell my healthcare provider before takingfinasteride tablets, USP?

Before takingfinasteride tablets, USP, tell your healthcare provider if you:

- have any other medical conditions, including problems with your prostate or liver

Tell your healthcare provider about all the medicines you take, including prescription and non- prescription medicines, vitamins, and herbal supplements.

Know the medicines you take. Keep a list of them to show your healthcare provider and pharmacist when you get a new medicine.

How should I takefinasteride tablets, USP?

- Take finasteride tablets, USP exactly as your healthcare provider tells you to take it.
- You may take finasteride tablets, USP with or without food.
- If you forget to take finasteride tablets, USP, do nottake an extra tablet. Just take the next tablet as usual.

Finasteride tablets, USP will not work faster or better if you take it more than once a day.

What are the possible side effects of Finasteride tablets, USP?

- decrease in your blood Prostate Specific Antigen (PSA) levels. Finasteride tablets, USP can affect a blood test called PSA (Prostate-Specific Antigen) for the screening of prostate cancer. If you have a PSA test done you should tell your healthcare provider that you are taking finasteride tablets, USP because finasteride tablets, USP decreases PSA levels. Changes in PSA levels will need to be evaluated by your healthcare provider. Any increase in follow-up PSA levels from their lowest point may signal the presence of prostate cancer and should be evaluated, even if the test results are still within the normal range for men not taking finasteride tablets, USP. You should also tell your healthcare provider if you have not been taking finasteride tablets, USP as prescribed because this may affect the PSA test results. For more information, talk to your healthcare provider.
- There may be an increased risk of a more serious form of prostate cancer in men taking finasteride at 5 times the dose of finasteride tablets, USP.

The most common side effects of finasteride tablets, USP include:

- decrease in sex drive
- trouble getting or keeping an erection
- a decrease in the amount of semen

The following have been reported in general use with finasteride tablets, USP:

- breast tenderness and enlargement. Tell your healthcare provider about any changes in your breasts such as lumps, pain or nipple discharge.
- depression;
- decrease in sex drive that continued after stopping the medication;
- allergic reactions including rash, itching, hives and swelling of the lips, tongue, throat, and face;
- problems with ejaculation that continued after stopping medication;
- testicular pain;
- difficulty in achieving an erection that continued after stopping the medication;
- male infertility and/or poor quality of semen.
- in rare cases, male breast cancer.

Tell your healthcare provider if you have any side effect that bothers you or that does not go away.

These are not all the possible side effects of finasteride tablets, USP. For more information, ask your healthcare provider or pharmacist.

Call your doctor for medical advice about side effects. You may report side effects to FDA at 1-800-FDA-1088.

How should I store Finasteride Tablets, USP 1 mg?

- Store finasteride tablets, USP at room temperature between 68˚F to 77˚F (20˚C to 25˚C).
- Keep Finasteride Tablets, USP 1 mg in a closed container and keep finasteride tablets, USP dry (protect from moisture).

Keepfinasteride tablets, USPand all medicines out of the reach of children.

General information about the safe and effective use offinasteride tablets, USP.

Medicines are sometimes prescribed for purposes other than those listed in this Patient Information leaflet. Do not use finasteride tablets, USP for a condition for which it was not prescribed. Do not give finasteride tablets, USP to other people, even if they have the same symptoms you have. It may harm them.

This Patient Information leaflet summarizes the most important information about finasteride tablets, USP. If you would like more information, talk with your healthcare provider. You can ask your pharmacist or healthcare provider for information about finasteride tablets, USP that is written for health professionals. For more information go to http://www.ascendlaboratories.com or call 1-877-272-7901.

What are the ingredients infinasteride tablets, USP?

Active ingredient: Finasteride, USP.

Inactive ingredients: hypromellose, iron oxide red, iron oxide yellow, lactose monohydrate, lauroylmacrogol 32 glycerides, magnesium stearate, microcrystalline cellulose, polyethylene glycol, pregelatinized starch, sodium starch glycolate, and titanium dioxide.

This Patient Information has been approved by the U.S. Food and Drug Administration.

For Patient Information, please visit:
http://www.ascendlaboratories.com/pti/finasteridetab1mg.pdf

Manufactured by:
Alkem Laboratories Ltd.,
Mumbai - 400 013, INDIA.
Distributed by:
Ascend Laboratories, LLC
Bedminster, NJ 07921
Revised: January 2025

PT 2328-05

PACKAGE LABEL

DRUG: Finasteride

GENERIC: Finasteride

DOSAGE: TABLET, COATED

ADMINSTRATION: ORAL

NDC: 70518-2287-0

NDC: 70518-2287-1

NDC: 70518-2287-2

COLOR: red

SHAPE: ROUND

SCORE: No score

SIZE: 7 mm

IMPRINT: F1

PACKAGING: 90 in 1 BOTTLE, PLASTIC

PACKAGING: 30 in 1 BOTTLE, PLASTIC

PACKAGING: 30 in 1 BLISTER PACK

ACTIVE INGREDIENT(S):

- FINASTERIDE 1mg in 1

INACTIVE INGREDIENT(S):

- LACTOSE MONOHYDRATE
- MICROCRYSTALLINE CELLULOSE
- STARCH, CORN
- SODIUM STARCH GLYCOLATE TYPE A POTATO
- MAGNESIUM STEARATE
- LAUROYL PEG-32 GLYCERIDES
- HYPROMELLOSE 2910 (6 MPA.S)
- TITANIUM DIOXIDE
- POLYETHYLENE GLYCOL 6000
- FERRIC OXIDE RED
- FERRIC OXIDE YELLOW